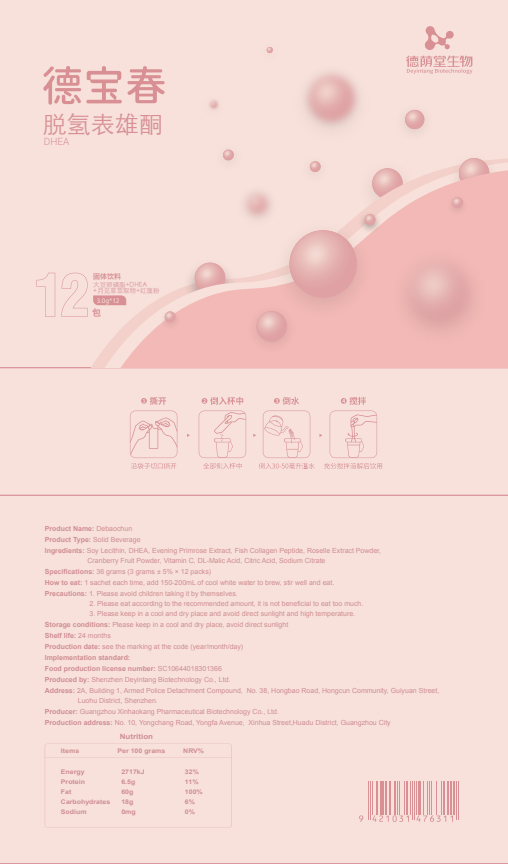 DRUG LABEL: Debaochun
NDC: 82570-016 | Form: POWDER
Manufacturer: Shenzhen Deyintang Biotechnology Co., Ltd.
Category: otc | Type: HUMAN OTC DRUG LABEL
Date: 20220222

ACTIVE INGREDIENTS: OENOTHERA BIENNIS WHOLE 5 g/100 g; COLLAGEN, SOLUBLE, FISH SKIN 10 g/100 g; .ALPHA.-TOCOPHEROL 2 dL/100 g; ASCORBIC ACID 2 g/100 g; LECITHIN, SOYBEAN 50 g/100 g; PRASTERONE 10 g/100 g; HIBISCUS SABDARIFFA CALYX 20 g/100 g
INACTIVE INGREDIENTS: BLUEBERRY; MALIC ACID; SODIUM CITRATE; CITRIC ACID MONOHYDRATE

ACTIVE INGREDIENT

Soy Lecithin, DHEA, Evening Primrose Extract,Fish Collagen Peptide, Roselle Extract Powder,Vitamin C,Vitamin E

INACTIVE INGREDIENT

Cranberry Fruit Powder,DL-Malic Acid,Citric Acid, Sodium Citrate

PURPOSE

health care

Please avoid children taking it by themselves.

How to eat

1 sachet each time, add 150-200mL of cool white water to brew,stir well and eat.

INDICATIONS AND USAGE

Please eat according to the recommended amount, it is not beneficial to eat too much.

Storage conditions

Please keep in a cool and dry place, avoid direct sunlight

WARNINGS

1.Please avoid children taking it by themselves.
2.Please eat according to the recommended amount, it is not beneficial to eat too much.

3.Please keep in a cool and dry place and avoid direct sunlight and high temperature.